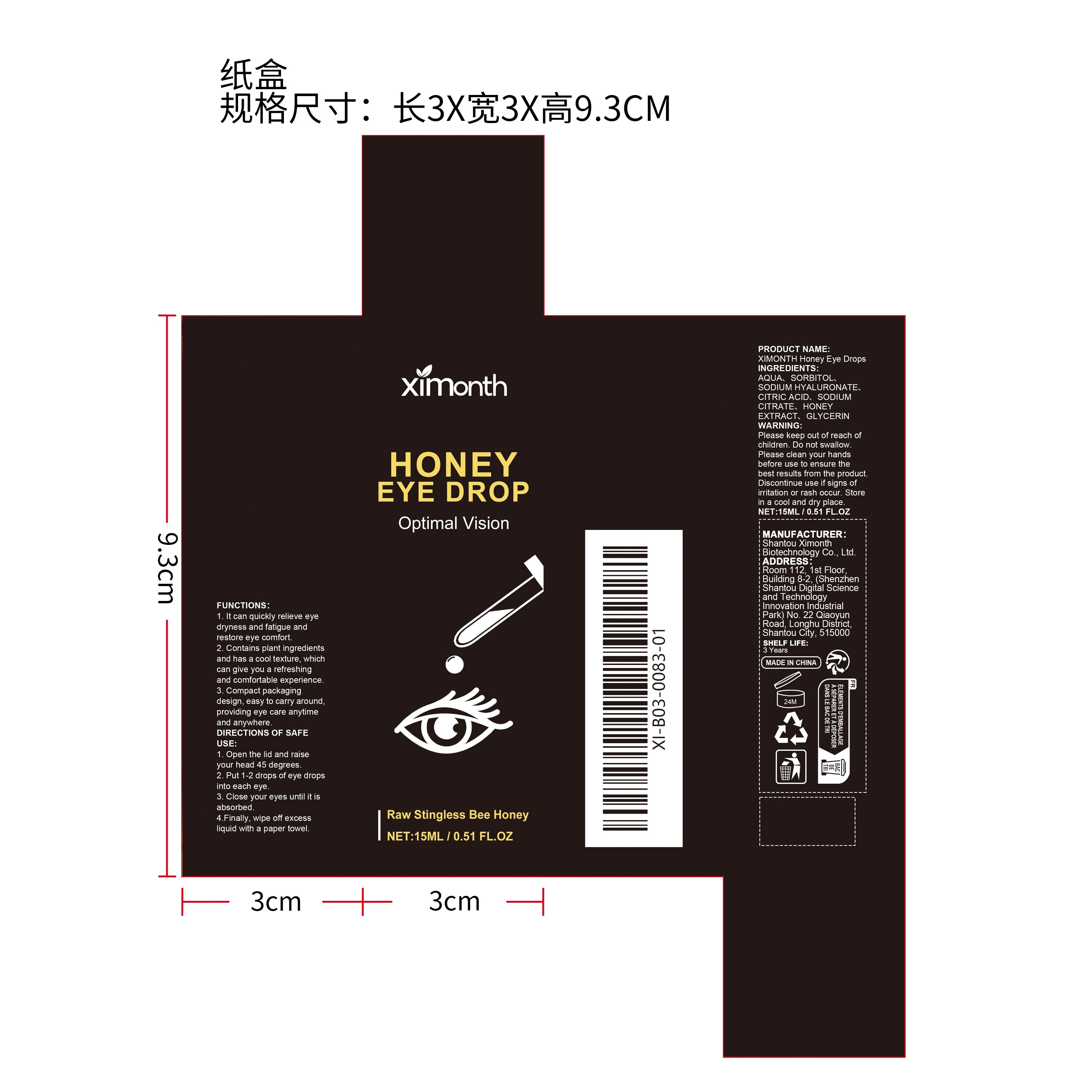 DRUG LABEL: XIMONTH Honey Eye Drops
NDC: 84989-014 | Form: LIQUID
Manufacturer: Shantou Ximonth Biotechnology Co., Ltd.
Category: otc | Type: HUMAN OTC DRUG LABEL
Date: 20251230

ACTIVE INGREDIENTS: HONEY 0.003 mg/15 mg
INACTIVE INGREDIENTS: CITRIC ACID 0.015 mg/15 mg; SODIUM HYALURONATE 0.045 mg/15 mg; GLYCERIN 0.003 mg/15 mg; SODIUM CITRATE 0.015 mg/15 mg; SORBITOL 0.15 mg/15 mg; AQUA 14.769 mg/15 mg

ACTIVE INGREDIENT

HONEY EXTRACT

PURPOSE

1. It can quickly relieve eye dryness and fatigue and restore eye comfort.

2. Contains plant ingredients and has a cool texture, which can give you a refreshing and comfortable experience.

3. Compact packaging design, easy to carry around, providing eye care anytime and anywhere.

WHEN USING

1. Open the lid and raise your head 45 degrees.

2. Put 1-2 drops of eye drops into each eye.

3. Close your eyes until it is absorbed.

4.Finally, wipe off excess liquid with a paper towel.

WARNINGS

Please keep out of reach of children. Do not swallow.Please clean your hands before use to ensure the best results from the product. Discontinue use if signs of irritation or rash occur. Store in a cool and dry place.

DO NOT USE

Discontinue use if signs of irritation or rash occur.

STOP USE

Discontinue use if signs of irritation or rash occur.

KEEP OUT OF REACH OF CHILDREN

Please keep out of reach of children. Do not swallow.

STORAGE AND HANDLING

Store in a cool and dry place.

INACTIVE INGREDIENT

AQUA、SORBITOL、SODIUM HYALURONATE、CITRIC ACID、SODIUM CITRATE、GLYCERIN

DOSAGE AND ADMINISTRATION

1. Open the lid and raise your head 45 degrees.

2. Put 1-2 drops of eye drops into each eye.

3. Close your eyes until it is absorbed.

4.Finally, wipe off excess liquid with a paper towel.

INDICATIONS AND USAGE

1. Open the lid and raise your head 45 degrees.

2. Put 1-2 drops of eye drops into each eye.

3. Close your eyes until it is absorbed.

4.Finally, wipe off excess liquid with a paper towel.